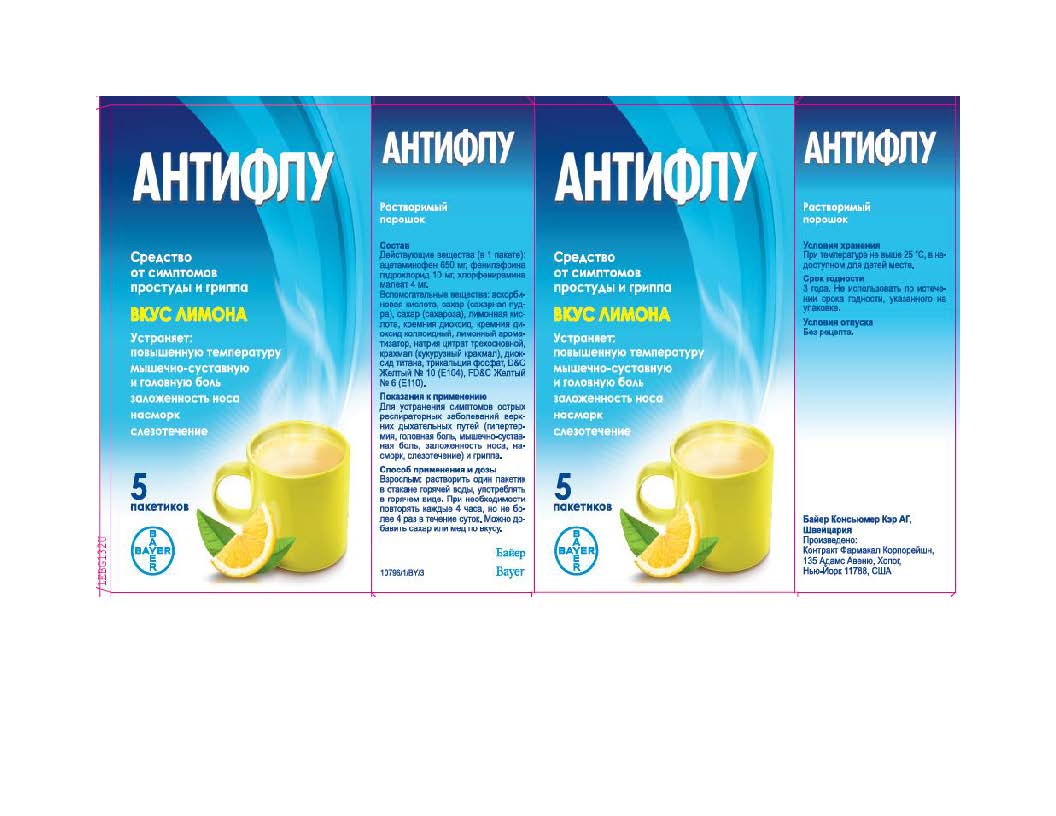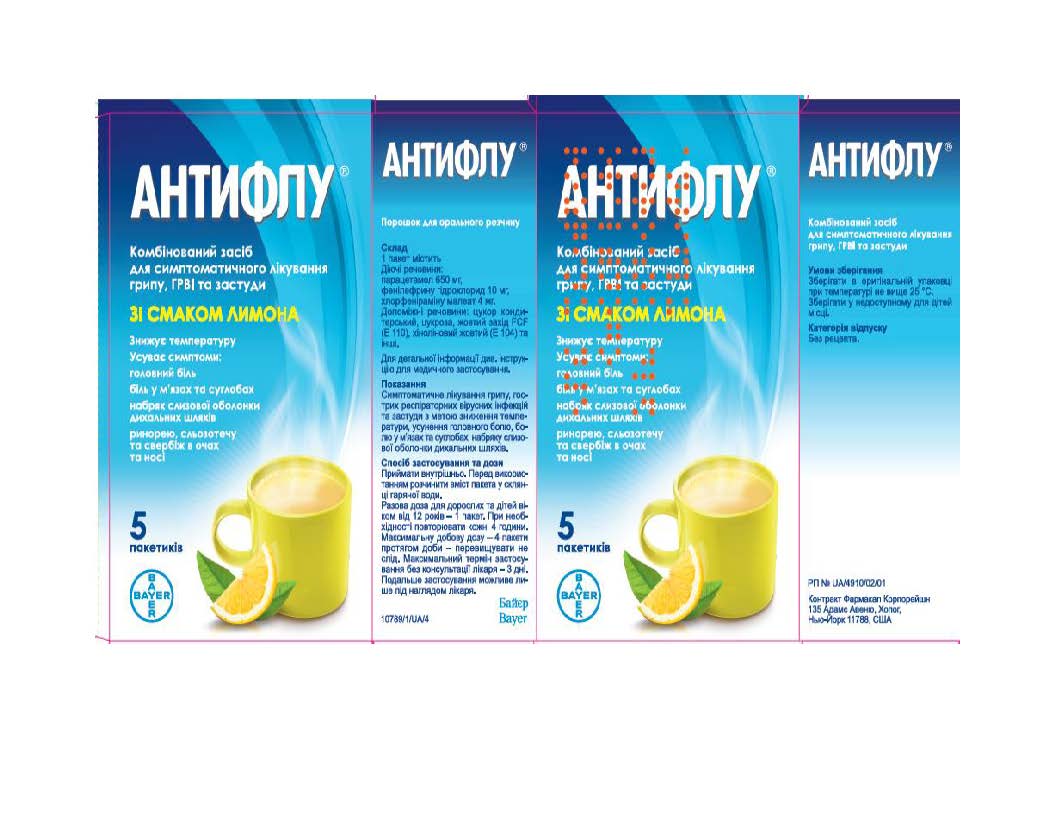 DRUG LABEL: Acetaminophen, Phenylephrine Hydrochloride, Chlorpheniramine Maleate
NDC: 10267-2657 | Form: POWDER, FOR SOLUTION
Manufacturer: Contract Pharmacal Corp.
Category: otc | Type: HUMAN OTC DRUG LABEL
Date: 20200402

ACTIVE INGREDIENTS: ACETAMINOPHEN 650 mg/17000 mg; PHENYLEPHRINE HYDROCHLORIDE 10 mg/17000 mg; CHLORPHENIRAMINE MALEATE 4 mg/17000 mg
INACTIVE INGREDIENTS: D&C YELLOW NO. 10; SUCROSE; TRICALCIUM PHOSPHATE; ANHYDROUS CITRIC ACID; FD&C YELLOW NO. 6; LEMON; ASCORBIC ACID; SILICON DIOXIDE; TRISODIUM CITRATE DIHYDRATE; STARCH, CORN; TITANIUM DIOXIDE

2657K- Export